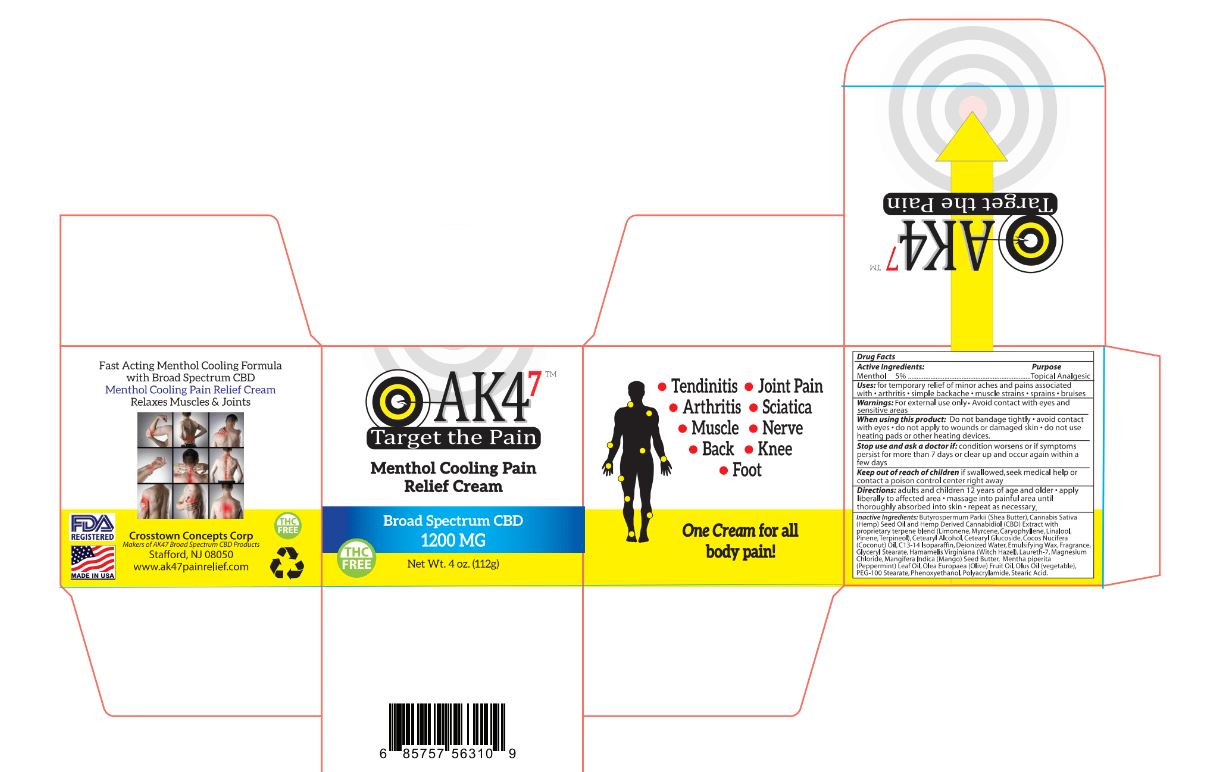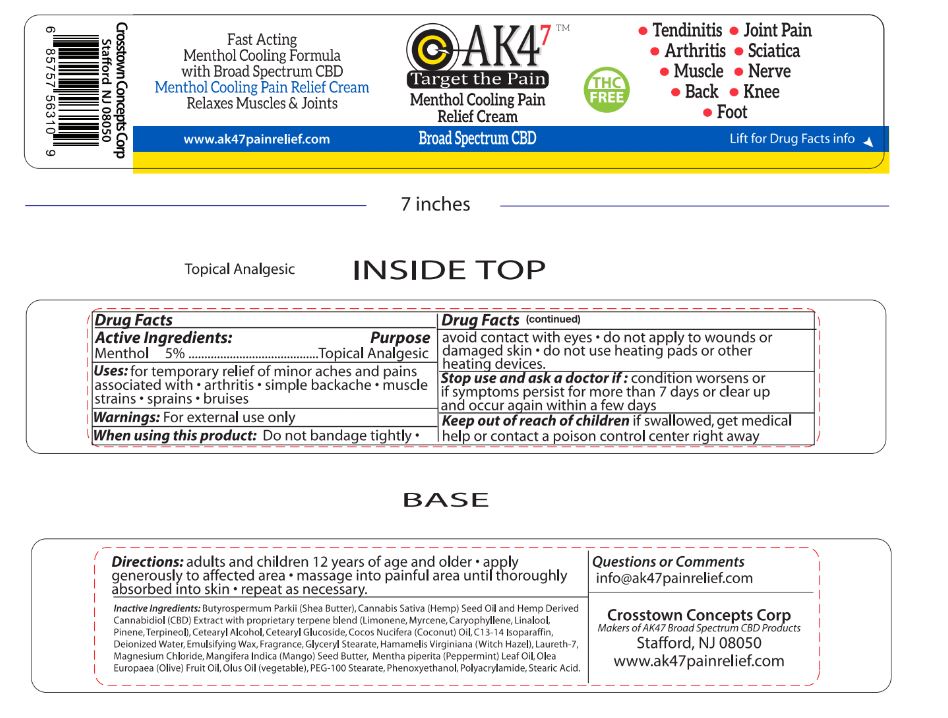 DRUG LABEL: AK47 MENTHOL WARMING
NDC: 90078-521 | Form: CREAM
Manufacturer: Crosstown Concepts Corporation
Category: otc | Type: HUMAN OTC DRUG LABEL
Date: 20200819

ACTIVE INGREDIENTS: MENTHOL 5.6 g/112 g
INACTIVE INGREDIENTS: LINALOOL, (+)-; CARYOPHYLLENE; PINENE; CETOSTEARYL ALCOHOL; C13-14 ISOPARAFFIN; LAURETH-7; MAGNESIUM CHLORIDE; CANNABIDIOL; LIMONENE, (+)-; STEARIC ACID; MANGIFERA INDICA SEED BUTTER; COCONUT OIL; PHENOXYETHANOL; POLYACRYLAMIDE (10000 MW); WITCH HAZEL; CORN OIL; MYRCENE; TERPINEOL; PEG-100 STEARATE; WHITE WAX; CETEARYL GLUCOSIDE; SHEA BUTTER; CANNABIS SATIVA SEED OIL; OLIVE OIL; PEPPERMINT OIL; WATER; GLYCERYL MONOSTEARATE; TABASCO PEPPER

AK4^7 Menthol Warming Pain Relief Cream

ACTIVE INGREDIENT

Menthol

5%

Stop use and ask a doctor if: condition worsens or if symptoms persist for more than 7 days or clear up and occur again within a few days.

Keep out of reach of children if swallowed, get medical help or contact a poison control center right away

PURPOSE

Topical Analgesic

Questions or Comments

info@ak47painrelief.com

When using this product: Do not bandage tightly

- avoid contact with eyes
- do not apply to wounds or damaged skin
- do not use heating pads or other heating devices.

WARNINGS

For external use only

INDICATIONS AND USAGE

Uses: for temporary relief of minor aches and pains associated with

- arthritis
- simple backache
- muscle strains
- sprains
- bruises

Directions

adults and children 12 years of age and older

- apply generously to affected area
- massage into painful area until thoroughy absorbed into skin
- repeat as necessary.

INACTIVE INGREDIENT

Butyrospermum Parkii (Shea Butter), Cannabis Sativa (Hemp) Seed Oil and Hemp Derived Cannabidiol (CBD) Extract with proprietary terpene blend (Limonene, Myrcene, Caryophyllene, Linalool, Pinene, Terpineol), Cetearyl Alcohol, Cetearyl Glucoside, Cocos Nucifera (Coconut) Oil, C13-14 Isoparaffin, Deionized Water, Emulsifying Wax, Fragrance, Glyceryl Stearate, Hamamelis Virginiana (Witch Hazel), Laureth-7, Magnesium Chloride, Mangifera Indica (Mango) Seed Butter, Mentha piperita (Peppermint) Leaf Oil, Olea Europaea (Olive) Fruit Oil, Olus Oil (vegetable), PEG-100 Stearate, Phenoxyethanol, Polyacrylamide, Stearic Acid.

COOLING CREAM LABEL

COOLING CREAM BOX